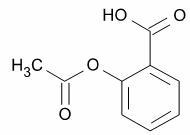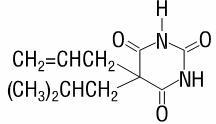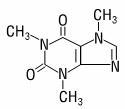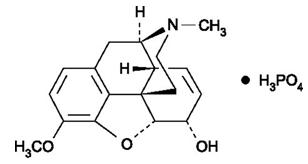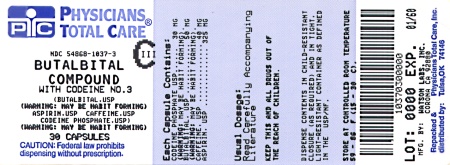 DRUG LABEL: Butalbital, Aspirin, Caffeine and Codeine Phosphate
NDC: 54868-1037 | Form: CAPSULE
Manufacturer: Physicians Total Care, Inc.
Category: prescription | Type: HUMAN PRESCRIPTION DRUG LABEL
Date: 20100629
DEA Schedule: CIII

ACTIVE INGREDIENTS: BUTALBITAL 50 mg/1 1; ASPIRIN 325 mg/1 1; CAFFEINE 40 mg/1 1; CODEINE PHOSPHATE 30 mg/1 1
INACTIVE INGREDIENTS: CELLULOSE, MICROCRYSTALLINE; STARCH, CORN; TALC; D&C YELLOW NO. 10; FD&C BLUE NO. 1; FD&C RED NO. 3; FD&C YELLOW NO. 6; GELATIN; TITANIUM DIOXIDE; FERRIC OXIDE RED

Rx only

DESCRIPTION

Butalbital, Aspirin, Caffeine, and Codeine Phosphate Capsules, USP is supplied in capsule form for oral administration.

Each capsule contains the following active ingredients:
butalbital, USP ……………………..50 mg
aspirin, USP ……………………....325 mg
caffeine, USP ………………………40 mg
codeine phosphate, USP …………30 mg

Butalbital (5-allyl-5-isobutylbarbituric acid) is a short- to intermediate-acting barbiturate. It has the following structural formula:

C11H16N2O3 molecular weight 224.26

Aspirin (benzoic acid, 2-(acetyloxy)-) is an analgesic, antipyretic, and anti-inflammatory. It has the following structural formula:

C9H8O4 molecular weight 180.16

Caffeine (1,3,7-trimethylxanthine) is a central nervous system stimulant. It has the following structural formula:

C8H10N4O2 molecular weight 194.19

Codeine phosphate (7,8-Didehydro-4,5α-epoxy-3-methoxy-17-methylmorphinan-6α-ol phosphate (1:1) (salt) hemihydrate) is a narcotic analgesic and antitussive. It has the following structural formula:

C18H24NO7P anhydrous molecular weight 397.37

Inactive Ingredients: microcrystalline cellulose, pregelatinized starch, talc. Gelatin capsules contain D&C Yellow No.10, FD&C Blue No.1, FD&C Red No. 3, FD&C Yellow No. 6, gelatin, titanium dioxide. The capsules are printed with edible ink containing red iron oxide.

CLINICAL PHARMACOLOGY

Butalbital, Aspirin, Caffeine, and Codeine Phosphate Capsules, USP is a combination drug product intended as a treatment for tension headache.

Butalbital, Aspirin, and Caffeine Capsules, USP consists of a fixed combination of caffeine 40 mg, butalbital 50 mg, and aspirin 325 mg. The role each component plays in the relief of the complex of symptoms known as tension headache is incompletely understood.

Pharmacokinetics

Bioavailability: The bioavailability of the components of the fixed combination of Butalbital, Aspirin, Caffeine, and Codeine Phosphate Capsules, USP is identical to their bioavailability when Butalbital, Aspirin, and Caffeine Capsules, USP and codeine are administered separately in equivalent molar doses.

The behavior of the individual components is described below.

Aspirin

The systemic availability of aspirin after an oral dose is highly dependent on the dosage form, the presence of food, the gastric emptying time, gastric pH, antacids, buffering agents, and particle size. These factors affect not necessarily the extent of absorption of total salicylates but more the stability of aspirin prior to absorption.

During the absorption process and after absorption, aspirin is mainly hydrolyzed to salicylic acid and distributed to all body tissues and fluids, including fetal tissues, breast milk, and the central nervous system (CNS). Highest concentrations are found in plasma, liver, renal cortex, heart, and lung. In plasma, about 50%-80% of the salicylic acid and its metabolites are loosely bound to plasma proteins.

The clearance of total salicylates is subject to saturable kinetics; however, first-order elimination kinetics are still a good approximation for doses up to 650 mg. The plasma half-life for aspirin is about 12 minutes and for salicylic acid and/or total salicylates is about 3 hours.

The elimination of therapeutic doses is through the kidneys either as salicylic acid or other biotransformation products. The renal clearance is greatly augmented by an alkaline urine as is produced by concurrent administration of sodium bicarbonate or potassium citrate.

The biotransformation of aspirin occurs primarily in the hepatocytes. The major metabolites are salicyluric acid (75%), the phenolic and acyl glucuronides of salicylate (15%), and gentisic and gentisuric acid (1%). The bioavailability of the aspirin component of Butalbital, Aspirin, Caffeine, and Codeine Phosphate Capsules, USP is equivalent to that of a solution except for a slower rate of absorption. A peak concentration of 8.8 mcg/mL was obtained at 40 minutes after a 650 mg dose.

See OVERDOSAGE for toxicity information.

Codeine

Codeine is readily absorbed from the gastrointestinal tract. It is rapidly distributed from the intravascular spaces to the various body tissues, with preferential uptake by parenchymatous organs such as the liver, spleen, and kidney. Codeine crosses the blood-brain barrier, and is found in fetal tissue and breast milk. The plasma concentration does not correlate with brain concentration or relief of pain, however, codeine is not bound to plasma proteins and does not accumulate in body tissues.

The plasma half-life is about 2.9 hours. The elimination of codeine is primarily via the kidneys, and about 90% of an oral dose is excreted by the kidneys within 24 hours of dosing. The urinary secretion products consist of free and glucuronide-conjugated codeine (about 70%), free and conjugated norcodeine (about 10%), free and conjugated morphine (about 10%), normorphine (4%), and hydrocodone (1%). The remainder of the dose is excreted in the feces.

At therapeutic doses, the analgesic effect reaches a peak within 2 hours and persists between 4 and 6 hours.

The bioavailability of the codeine component of Butalbital, Aspirin, Caffeine, and Codeine Phosphate Capsules, USP is equivalent to that of a solution. Peak concentrations of 198 ng/mL were obtained at 1 hour after a 60 mg dose.

See OVERDOSAGE for toxicity information.

Butalbital

Butalbital is well absorbed from the gastrointestinal tract and is expected to distribute to most of the tissues in the body. Barbiturates, in general, may appear in breast milk and readily cross the placental barrier. They are bound to plasma and tissue proteins to a varying degree and binding increases directly as a function of lipid solubility.

Elimination of butalbital is primarily via the kidney (59%-88% of the dose) as unchanged drug or metabolites. The plasma half-life is about 35 hours. Urinary excretion products included parent drug (about 3.6% of the dose), 5-isobutyl-5-(2,3-dihydroxypropyl) barbituric acid (about 24% of the dose), 5-allyl-5(3-hydroxy-2-methyl-1-propyl) barbituric acid (about 4.8% of the dose), products with the barbituric acid ring hydrolyzed with excretion of urea (about 14% of the dose), as well as unidentified materials. Of the material excreted in the urine, 32% was conjugated.

The bioavailability of the butalbital component of Butalbital, Aspirin, Caffeine, and Codeine Phosphate Capsules, USP is equivalent to that of a solution except for a decrease in the rate of absorption. A peak concentration of 2,020 ng/mL is obtained at about 1.5 hours after a 100 mg dose.

The in vitro plasma protein binding of butalbital is 45% over the concentration range of 0.5-20 mcg/mL. This falls within the range of plasma protein binding (20%-45%) reported with other barbiturates such as phenobarbital, pentobarbital, and secobarbital sodium. The plasma-to-blood concentration ratio was almost unity indicating that there is no preferential distribution of butalbital into either plasma or blood cells.

See OVERDOSAGE for toxicity information.

Caffeine

Like most xanthines, caffeine is rapidly absorbed and distributed in all body tissues and fluids, including the CNS, fetal tissues, and breast milk.

Caffeine is cleared rapidly through metabolism and excretion in the urine. The plasma half-life is about 3 hours. Hepatic biotransformation prior to excretion results in about equal amounts of 1-methylxanthine and 1-methyluric acid. Of the 70% of the dose that has been recovered in the urine, only 3% was unchanged drug.

The bioavailability of the caffeine component Butalbital, Aspirin, Caffeine, and Codeine Phosphate Capsules, USP is equivalent to that of a solution except for a slightly longer time to peak. A peak concentration of 1,660 ng/mL was obtained in less than an hour for an 80 mg dose.

See OVERDOSAGE for toxicity information.

INDICATIONS AND USAGE

Butalbital, Aspirin, Caffeine, and Codeine Phosphate Capsules, USP is indicated for the relief of the symptom complex of tension (or muscle contraction) headache.

Evidence supporting the efficacy of butalbital, aspirin, caffeine, and codeine phosphate capsules is derived from 2 multi-clinic trials that compared patients with tension headache randomly assigned to 4 parallel treatments: butalbital, aspirin, caffeine, and codeine phosphate capsules; codeine; Butalbital, Aspirin, and Caffeine Capsules, USP; and placebo. Response was assessed over the course of the first 4 hours of each of 2 distinct headaches, separated by at least 24 hours. Butalbital, aspirin, caffeine, and codeine phosphate capsules proved statistically significantly superior to each of its components (Butalbital, Aspirin, and Caffeine Capsules, USP and codeine) and to placebo on measures of pain relief.

Evidence supporting the efficacy and safety of Butalbital, Aspirin, Caffeine, and Codeine Phosphate Capsules, USP in the treatment of multiple recurrent headaches is unavailable. Caution in this regard is required because codeine and butalbital are habit-forming and potentially abusable.

CONTRAINDICATIONS

Butalbital, Aspirin, Caffeine, and Codeine Phosphate Capsules, USP is contraindicated under the following conditions:

1. Hypersensitivity or intolerance to aspirin, caffeine, butalbital or codeine.
2. Patients with a hemorrhagic diathesis (e.g., hemophilia, hypoprothrombinemia, von Willebrand’s disease, the thrombocytopenias, thrombasthenia and other ill-defined hereditary platelet dysfunctions, severe vitamin K deficiency and severe liver damage).
3. Patients with the syndrome of nasal polyps, angioedema and bronchospastic reactivity to aspirin or other nonsteroidal anti-inflammatory drugs. Anaphylactoid reactions have occurred in such patients.
4. Peptic ulcer or other serious gastrointestinal lesions.
5. Patients with porphyria.

WARNINGS

Therapeutic doses of aspirin can cause anaphylactic shock and other severe allergic reactions. It should be ascertained if the patient is allergic to aspirin, although a specific history of allergy may be lacking.

Significant bleeding can result from aspirin therapy in patients with peptic ulcer or other gastrointestinal lesions, and in patients with bleeding disorders.

Aspirin administered pre-operatively may prolong the bleeding time.

In the presence of head injury or other intracranial lesions, the respiratory depressant effects of codeine and other narcotics may be markedly enhanced, as well as their capacity for elevating cerebrospinal fluid pressure. Narcotics also produce other CNS depressant effects, such as drowsiness, that may further obscure the clinical course of patients with head injuries.

Codeine or other narcotics may obscure signs on which to judge the diagnosis or clinical course of patients with acute abdominal conditions.

Butalbital and codeine are both habit-forming and potentially abusable. Consequently, the extended use of Butalbital, Aspirin, Caffeine, and Codeine Phosphate Capsules, USP is not recommended.

Results from epidemiologic studies indicate an association between aspirin and Reye’s Syndrome. Caution should be used in administering this product to children, including teenagers, with chicken pox or flu.

PRECAUTIONS

General

Butalbital, Aspirin, Caffeine, and Codeine Phosphate Capsules, USP should be prescribed with caution for certain special-risk patients such as the elderly or debilitated, and those with severe impairment of renal or hepatic function, coagulation disorders, or head injuries, elevated intracranial pressure, acute abdominal conditions, hypothyroidism, urethral stricture, Addison’s disease, prostatic hypertrophy, and peptic ulcer.

Aspirin should be used with caution in patients on anticoagulant therapy and in patients with underlying hemostatic defects.

Precautions should be taken when administering salicylates to persons with known allergies. Hypersensitivity to aspirin is particularly likely in patients with nasal polyps, and relatively common in those with asthma.

Ultra-rapid Metabolizers of Codeine

Some individuals may be ultra-rapid metabolizers due to a specific CYP2D6*2x2 genotype. These individuals convert codeine into its active metabolite, morphine, more rapidly and completely than other people. This rapid conversion results in higher than expected serum morphine levels. Even at labeled dosage regimens, individuals who are ultra-rapid metabolizers may experience overdose symptoms such as extreme sleepiness, confusion or shallow breathing.

The prevalence of this CYP2D6 phenotype varies widely and has been estimated at 0.5 to 1% in Chinese and Japanese, 0.5 to 1% in Hispanics, 1-10% in Caucasians, 3% in African Americans, and 16-28% in North Africans, Ethiopians and Arabs. Data is not available for other ethnic groups.

When physicians prescribe codeine-containing drugs, they should choose the lowest effective dose for the shortest period of time and should inform their patients about these risks and the signs of morphine overdose. (See PRECAUTIONS, Nursing Mothers)

Information for Patients

Patients should be informed that Butalbital, Aspirin, Caffeine, and Codeine Phosphate Capsules, USP contains aspirin and should not be taken by patients with an aspirin allergy.

Butalbital, Aspirin, Caffeine, and Codeine Phosphate Capsules, USP may impair the mental and/or physical abilities required for performance of potentially hazardous tasks such as driving a car or operating machinery. Such tasks should be avoided while taking Butalbital, Aspirin, Caffeine, and Codeine Phosphate Capsules, USP.

Alcohol and other CNS depressants may produce an additive CNS depression when taken with Butalbital, Aspirin, Caffeine, and Codeine Phosphate Capsules, USP, and should be avoided.

Codeine and butalbital may be habit-forming. Patients should take the drug only for as long as it is prescribed, in the amounts prescribed, and no more frequently than prescribed.

For information on use in geriatric patients, refer to PRECAUTIONS, Geriatric Use.

Caution patients that some people have a variation in a liver enzyme and change codeine into morphine more rapidly and completely than other people. These people are ultra-rapid metabolizers and are more likely to have higher-than-normal levels of morphine in their blood after taking codeine which can result in overdose symptoms such as extreme sleepiness, confusion, or shallow breathing. In most cases, it is unknown if someone is an ultra-rapid codeine metabolizer.

Nursing mothers taking codeine can also have higher morphine levels in their breast milk if they are ultra-rapid metabolizers. These higher levels of morphine in breast milk may lead to life-threatening or fatal side effects in nursing babies. Instruct nursing mothers to watch for signs of morphine toxicity in their infants including increased sleepiness (more than usual), difficulty breastfeeding, breathing difficulties, or limpness. Instruct nursing mothers to talk to the baby's doctor immediately if they notice these signs and, if they cannot reach the doctor right away, to take the baby to an emergency room or call 911 (or local emergency services).

Laboratory Tests

In patients with severe hepatic or renal disease, effects of therapy should be monitored with serial liver and/or renal function tests.

Drug Interactions

The CNS effects of butalbital may be enhanced by monoamine oxidase (MAO) inhibitors.

In patients receiving concomitant corticosteroids and chronic use of aspirin, withdrawal of corticosteroids may result in salicylism because corticosteroids enhance renal clearance of salicylates and their withdrawal is followed by return to normal rates of renal clearance.

Butalbital, Aspirin, Caffeine, and Codeine Phosphate Capsules, USP may enhance the effects of:

1. Oral anticoagulants, causing bleeding by inhibiting prothrombin formation in the liver and displacing anticoagulants from plasma protein binding sites.
2. Oral antidiabetic agents and insulin, causing hypoglycemia by contributing an additive effect, if dosage of Butalbital, Aspirin, Caffeine, and Codeine Phosphate Capsules, USP exceeds maximum recommended daily dosage.
3. 6-mercaptopurine and methotrexate, causing bone marrow toxicity and blood dyscrasias by displacing these drugs from secondary binding sites, and, in the case of methotrexate, also reducing its excretion.
4. Non-steroidal anti-inflammatory agents, increasing the risk of peptic ulceration and bleeding by contributing additive effects.
5. Other narcotic analgesics, alcohol, general anesthetics, tranquilizers such as chlordiazepoxide, sedative-hypnotics, or other CNS depressants, causing increased CNS depression.

Butalbital, Aspirin, Caffeine, and Codeine Phosphate Capsules, USP may diminish the effects of:

Uricosuric agents such as probenecid and sulfinpyrazone, reducing their effectiveness in the treatment of gout. Aspirin competes with these agents for protein binding sites.

Drug/Laboratory Test Interactions

Aspirin: Aspirin may interfere with the following laboratory determinations in blood: serum amylase, fasting blood glucose, cholesterol, protein, serum glutamic-oxalacetic transaminase (SGOT), uric acid, prothrombin time and bleeding time. Aspirin may interfere with the following laboratory determinations in urine: glucose, 5-hydroxy-indoleacetic acid, Gerhardt ketone, vanillylmandelic acid (VMA), uric acid, diacetic acid, and spectrophotometric detection of barbiturates.

Codeine: Codeine may increase serum amylase levels.

Carcinogenesis, Mutagenesis, Impairment of Fertility

Adequate long-term studies have been conducted in mice and rats with aspirin, alone or in combination with other drugs, in which no evidence of carcinogenesis was seen. No adequate studies have been conducted in animals to determine whether aspirin has a potential for mutagenesis or impairment of fertility. No adequate studies have been conducted in animals to determine whether butalbital has a potential for carcinogenesis, mutagenesis, or impairment of fertility.

Usage in Pregnancy Teratogenic Effects

Pregnancy Category C. Animal reproduction studies have not been conducted with Butalbital, Aspirin, Caffeine, and Codeine Phosphate Capsules, USP. It is also not known whether Butalbital, Aspirin, Caffeine, and Codeine Phosphate Capsules, USP can cause fetal harm when administered to a pregnant woman or can affect reproduction capacity. Butalbital, Aspirin, Caffeine, and Codeine Phosphate Capsules, USP should be given to a pregnant woman only when clearly needed.

Nonteratogenic Effects

Although Butalbital, Aspirin, Caffeine, and Codeine Phosphate Capsules, USP was not implicated in the birth defect, a female infant was born with lissencephaly, pachygyria and heterotopic gray matter. The infant was born 8 weeks prematurely to a woman who had taken an average of 90 butalbital, aspirin, caffeine, and codeine phosphate capsules each month from the first few days of pregnancy. The child’s development was mildly delayed and from one year of age she had partial simple motor seizures.

Withdrawal seizures were reported in a two-day-old male infant whose mother had taken a butalbital-containing drug during the last 2 months of pregnancy. Butalbital was found in the infant’s serum. The infant was given phenobarbital 5 mg/kg, which was tapered without further seizure or other withdrawal symptoms.

Studies of aspirin use in pregnant women have not shown that aspirin increases the risk of abnormalities when administered during the first trimester of pregnancy. In controlled studies involving 41,337 pregnant women and their offspring, there was no evidence that aspirin taken during pregnancy caused stillbirth, neonatal death or reduced birth weight. In controlled studies of 50,282 pregnant women and their offspring, aspirin administration in moderate and heavy doses during the first four lunar months of pregnancy showed no teratogenic effect.

Reproduction studies have been performed in rabbits and rats at doses up to 150 times the human dose and have revealed no evidence of impaired fertility or harm to the fetus due to codeine.

Therapeutic doses of aspirin in pregnant women close to term may cause bleeding in mother, fetus, or neonate. During the last 6 months of pregnancy, regular use of aspirin in high doses may prolong pregnancy and delivery.

Labor and Delivery

Ingestion of aspirin prior to delivery may prolong delivery or lead to bleeding in the mother or neonate. Use of codeine during labor may lead to respiratory depression in the neonate.

Nursing Mothers

Aspirin, caffeine, barbiturates and codeine are excreted in breast milk in small amounts, but the significance of their effects on nursing infants is not known. Because of potential for serious adverse reactions in nursing infants from Butalbital, Aspirin, Caffeine, and Codeine Phosphate Capsules, USP, a decision should be made whether to discontinue nursing or to discontinue the drug, taking into account the importance of the drug to the mother.

Codeine is secreted into human milk. In women with normal codeine metabolism (normal CYP2D6 activity), the amount of codeine secreted into human milk is low and dose-dependent. Despite the common use of codeine products to manage postpartum pain, reports of adverse events in infants are rare. However, some women are ultra-rapid metabolizers of codeine. These women achieve higher-than-expected serum levels of codeine's active metabolite, morphine, leading to higher-than-expected levels of morphine in breast milk and potentially dangerously high serum morphine levels in their breastfed infants. Therefore, maternal use of codeine can potentially lead to serious adverse reactions, including death, in nursing infants.

The prevalence of this CYP2D6 phenotype varies widely and has been estimated at 0.5 to 1% in Chinese and Japanese, 0.5 to 1% in Hispanics, 1-10% in Caucasians, 3% in African Americans, and 16-28% in North Africans, Ethiopians and Arabs. Data is not available for other ethnic groups.

The risk of infant exposure to codeine and morphine through breast milk should be weighed against the benefits of breastfeeding for both the mother and baby. Caution should be exercised when codeine is administered to a nursing woman. If a codeine containing product is selected, the lowest dose should be prescribed for the shortest period of time to achieve the desired clinical effect. Mothers using codeine should be informed about when to seek immediate medical care and how to identify the signs and symptoms of neonatal toxicity, such as drowsiness or sedation, difficulty breastfeeding, breathing difficulties, and decreased tone, in their baby. Nursing mothers who are ultra-rapid metabolizers may also experience overdose symptoms such as extreme sleepiness, confusion or shallow breathing. Prescribers should closely monitor mother-infant pairs and notify treating pediatricians about the use of codeine during breastfeeding. (See PRECAUTIONS, General, Ultra-rapid Metabolizers of Codeine)

Pediatric Use

Safety and effectiveness in pediatric patients have not been established.

Geriatric Use

Clinical studies of butalbital, aspirin, caffeine, and codeine phosphate capsules did not include sufficient numbers of subjects aged 65 and over to determine whether they respond differently from younger subjects. Other reported clinical experience has not identified differences in responses between the elderly and younger patients. In general, dose selection for an elderly patient should be cautious, usually starting at the low end of the dosing range, reflecting the greater frequency of decreased hepatic, renal, or cardiac function, and of concomitant disease or other drug therapy.

Butalbital is known to be substantially excreted by the kidney, and the risk of toxic reactions to this drug may be greater in patients with impaired renal function. Because elderly patients are more likely to have decreased renal function, care should be taken in dose selection, and it may be useful to monitor renal function.

ADVERSE REACTIONS

Commonly Observed

The most commonly reported adverse events associated with the use of butalbital, aspirin, caffeine, and codeine phosphate capsules and not reported at an equivalent incidence by placebo-treated patients were nausea and/or abdominal pain, drowsiness, and dizziness.

Associated with Treatment Discontinuation

Of the 382 patients treated with butalbital, aspirin, caffeine, and codeine phosphate capsules in controlled clinical trials, three (0.8%) discontinued treatment with butalbital, aspirin, caffeine, and codeine phosphate capsules because of adverse events. One patient each discontinued treatment for the following reasons: gastrointestinal upset; lightheadedness and heavy eyelids; and drowsiness and generalized tingling.

Incidence in Controlled Clinical Trials

The following table summarizes the incidence rates of the adverse events reported by at least 1% of the butalbital, aspirin, caffeine, and codeine phosphate capsules treated patients in controlled clinical trials comparing butalbital, aspirin, caffeine, and codeine phosphate capsules to placebo, and provides a comparison to the incidence rates reported by the placebo-treated patients.

The prescriber should be aware that these figures cannot be used to predict the incidence of side effects in the course of usual medical practice where patient characteristics and other factors differ from those that prevailed in the clinical trials. Similarly, the cited frequencies cannot be compared with figures obtained from other clinical investigations involving different treatments, uses, and investigators.

Adverse Events Reported by at Least 1% of Butalbital, Aspirin, Caffeine, and Codeine Phosphate Capsules Treated Patients During Placebo Controlled Clinical Trials Incidence Rate of Adverse Events
Body System/ Adverse Event | Butalbital, Aspirin, Caffeine, and Codeine Phosphate Capsules (N = 382) | Placebo (N = 377)
Central Nervous Drowsiness | 2.4% | 0.5%
Dizziness/Lightheadedness | 2.6% | 0.5%
Intoxicated Feeling | 1.0% | 0%
Gastrointestinal Nausea/Abdominal Pain | 3.7% | 0.8%

Other Adverse Events Reported During Controlled Clinical Trials

The listing that follows represents the proportion of the 382 patients exposed to butalbital, aspirin, caffeine, and codeine phosphate capsules while participating in the controlled clinical trials who reported, on at least one occasion, an adverse event of the type cited. All reported adverse events, except those already presented in the previous table, are included. It is important to emphasize that, although the adverse events reported did occur while the patient was receiving butalbital, aspirin, caffeine, and codeine phosphate capsules, the adverse events were not necessarily caused by butalbital, aspirin, caffeine, and codeine phosphate capsules.

Adverse events are classified by body system and frequency. “Frequent” is defined as an adverse event which occurred in at least 1/100 (1%) of the patients; all adverse events listed in the previous table are frequent. “Infrequent” is defined as an adverse event that occurred in less than 1/100 patients but at least 1/1000 patients. All adverse events tabulated below are classified as infrequent.

Central Nervous: headache, shaky feeling, tingling, agitation, fainting, fatigue, heavy eyelids, high energy, hot spells, numbness, and sluggishness.

Autonomic Nervous: dry mouth and hyperhidrosis.

Gastrointestinal: vomiting, difficulty swallowing, and heartburn.

Cardiovascular: tachycardia.

Musculoskeletal: leg pain and muscle fatigue.

Genitourinary: diuresis.

Miscellaneous: pruritus, fever, earache, nasal congestion, and tinnitus.

Voluntary reports of adverse drug events, temporally associated with butalbital, aspirin, caffeine, and codeine phosphate capsules, that have been received since market introduction and that were not reported in clinical trials by the patients treated with butalbital, aspirin, caffeine, and codeine phosphate capsules, are listed below. Many or most of these events may have no causal relationship with the drug and are listed according to body system.

Central Nervous: Abuse, addiction, anxiety, depression, disorientation, hallucination, hyperactivity, insomnia, libido decrease, nervousness, neuropathy, psychosis, sedation, sexual activity increase, slurred speech, twitching, unconsciousness, vertigo.

Autonomic Nervous: epistaxis, flushing, miosis, salivation.

Gastrointestinal: anorexia, appetite increased, constipation, diarrhea, esophagitis, gastroenteritis, gastrointestinal spasm, hiccup, mouth burning, pyloric ulcer.

Cardiovascular: chest pain, hypotensive reaction, palpitations, syncope.

Skin: erythema, erythema multiforme, exfoliative dermatitis, hives, rash, toxic epidermal necrolysis.

Urinary: kidney impairment, urinary difficulty.

Miscellaneous: allergic reaction, anaphylactic shock, cholangiocarcinoma, drug interaction with erythromycin (stomach upset), edema.

The following adverse drug events may be borne in mind as potential effects of the components of Butalbital, Aspirin, Caffeine, and Codeine Phosphate Capsules, USP. Potential effects of high dosage are listed in the OVERDOSAGE section of this insert.

Aspirin: occult blood loss, hemolytic anemia, iron deficiency anemia, gastric distress, heartburn, nausea, peptic ulcer, prolonged bleeding time, acute airway obstruction, renal toxicity when taken in high doses for prolonged periods, impaired urate excretion, hepatitis.

Caffeine: cardiac stimulation, irritability, tremor, dependence, nephrotoxicity, hyperglycemia.

Codeine: nausea, vomiting, drowsiness, lightheadedness, constipation, pruritus.

DRUG ABUSE AND DEPENDENCE

Controlled Substance

Butalbital, Aspirin, Caffeine, and Codeine Phosphate Capsules, USP is controlled by the Drug Enforcement Administration and is classified under Schedule III.

Abuse and Dependence

Codeine

Codeine can produce drug dependence of the morphine type and, therefore, has the potential for being abused. Psychological dependence, physical dependence, and tolerance may develop upon repeated administration and it should be prescribed and administered with the same degree of caution appropriate to the use of other oral narcotic medications.

Butalbital

Barbiturates may be habit-forming: Tolerance, psychological dependence, and physical dependence may occur especially following prolonged use of high doses of barbiturates. The average daily dose for the barbiturate addict is usually about 1,500 mg. As tolerance to barbiturates develops, the amount needed to maintain the same level of intoxication increases; tolerance to a fatal dosage, however, does not increase more than twofold. As this occurs, the margin between an intoxication dosage and fatal dosage becomes smaller. The lethal dose of a barbiturate is far less if alcohol is also ingested. Major withdrawal symptoms (convulsions and delirium) may occur within 16 hours and last up to 5 days after abrupt cessation of these drugs. Intensity of withdrawal symptoms gradually declines over a period of approximately 15 days. Treatment of barbiturate dependence consists of cautious and gradual withdrawal of the drug. Barbiturate-dependent patients can be withdrawn by using a number of different withdrawal regimens. One method involves initiating treatment at the patient’s regular dosage level and gradually decreasing the daily dosage as tolerated by the patient.

OVERDOSAGE

The toxic effects of acute overdosage of Butalbital, Aspirin, Caffeine, and Codeine Phosphate Capsules, USP are attributable mainly to the barbiturate and codeine components, and, to a lesser extent, aspirin. Because toxic effects of caffeine occur in very high dosages only, the possibility of significant caffeine toxicity from Butalbital, Aspirin, Caffeine, and Codeine Phosphate Capsules, USP overdosage is unlikely.

Signs and Symptoms

Symptoms attributable to acute barbiturate poisoning include drowsiness, confusion, and coma; respiratory depression; hypotension; hypovolemic shock. Symptoms attributable to acute aspirin poisoning include hyperpnea; acid-base disturbances with development of metabolic acidosis; vomiting and abdominal pain; tinnitus, hyperthermia; hypoprothrombinemia; restlessness; delirium; convulsions. Acute caffeine poisoning may cause insomnia, restlessness, tremor, and delirium; tachycardia and extrasystoles. Symptoms of acute codeine poisoning include the opioid triad of: pinpoint pupils, marked depression of respiration, and loss of consciousness. Convulsions may occur.

Treatment

The following paragraphs describe one approach to the treatment of overdose with Butalbital, Aspirin, Caffeine, and Codeine Phosphate Capsules, USP. However, because strategies for the management of an overdose continually evolve, consultation with a regional poison control center is strongly encouraged.

Treatment consists primarily of management of barbiturate intoxication, reversal of the effects of codeine, and the correction of the acid-base imbalance due to salicylism. Vomiting should be induced mechanically or with emetics in the conscious patient. Gastric lavage may be used if the pharyngeal and laryngeal reflexes are present and if less than 4 hours have elapsed since ingestion. A cuffed endotracheal tube should be inserted before gastric lavage of the unconscious patient and when necessary to provide assisted respiration. Diuresis, alkalinization of the urine, and correction of electrolyte disturbances should be accomplished through administration of intravenous fluids such as 1% sodium bicarbonate and 5% dextrose in water.

Meticulous attention should be given to maintaining adequate pulmonary ventilation. The value of vasopressor agents such as Norepinephrine or Phenylephrine Hydrochloride in treating hypotension is questionable since they increase vasoconstriction and decrease blood flow. However, if prolonged support of blood pressure is required, Norepinephrine Bitartrate (Levophed®) may be given I.V. with the usual precautions and serial blood pressure monitoring. In severe cases of intoxication, peritoneal dialysis, hemodialysis, or exchange transfusion may be lifesaving. Hypoprothrombinemia should be treated with vitamin K, intravenously.

Methemoglobinemia over 30% should be treated with methylene blue by slow intravenous administration.

Naloxone, a narcotic antagonist, can reverse respiratory depression and coma associated with opioid overdose. Typically, a dose of 0.4-2 mg is given parenterally and may be repeated if an adequate response is not achieved. Since the duration of action of codeine may exceed that of the antagonist, the patient should be kept under continued surveillance and repeated doses of the antagonist should be administered as needed to maintain adequate respiration. A narcotic antagonist should not be administered in the absence of clinically significant respiratory or cardiovascular depression.

Up-to-date information about the treatment of overdose can be obtained from a Certified Regional Poison Control Center. Telephone numbers of Certified Regional Poison Control Centers are listed in the Physicians’ Desk Reference®.

Toxic and Lethal Doses (for adults)

Butalbital: toxic dose 1 g (20 capsules); lethal dose 2-5 g
Aspirin: toxic blood level greater than 30 mg/100 mL; lethal dose 10-30 g
Caffeine: toxic dose greater than 1 g; (25 capsules); lethal dose unknown
Codeine: toxic dose 240 mg (8 capsules); lethal dose 0.5-1 g

DOSAE AND ADMINISTRATION

One or 2 capsules every 4 hours. Total daily dosage should not exceed 6 capsules.

Extended and repeated use of this product is not recommended because of the potential for physical dependence.

HOW SUPPLIED

Butalbital, Aspirin, Caffeine, and Codeine Phosphate Capsules, USP
Blue cap with a yellow body. Cap is imprinted with “WATSON” in red. Body is imprinted with “3546” in red. Supplied in:

bottles of 20 NDC 54868-1037-1

bottles of 30 NDC 54868-1037-3

bottles of 60 NDC 54868-1037-5

bottles of 120 NDC 54868-1037-4

which are supplied with child-resistant closures.

Store and Dispense

Below 25°C (77°F); tight container. Protect from moisture.

Rx only

Watson Laboratories, Inc.
Corona, CA 92880 USA

Revised: January 2007

BASPCC01/07
S0107

Relabeling and Repackaging by:
Physicians Total Care, Inc.
Tulsa, OK 74146

PRINCIPAL DISPLAY PANEL

Butalbital, Aspirin, Caffeine, and Codeine Phosphate Capsules, USP

50 mg/325 mg/40 mg/30 mg